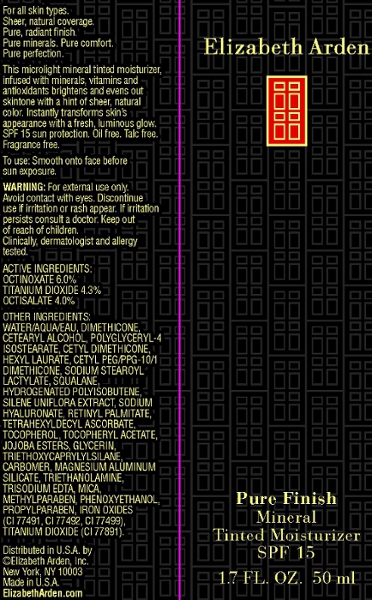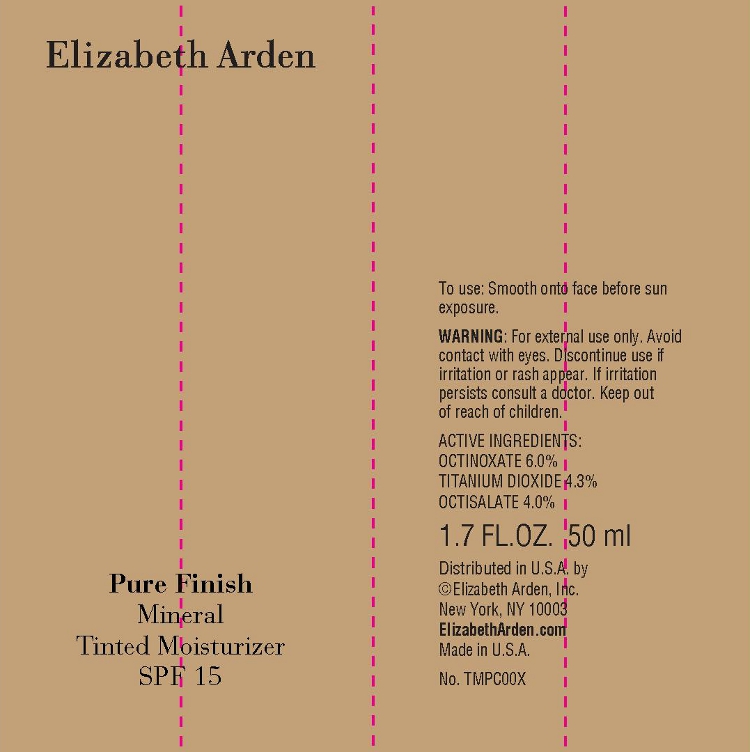 DRUG LABEL: Pure Finish Mineral Tinted Moisturizer SPF 15
NDC: 67938-110 | Form: LOTION
Manufacturer: Elizabeth Arden, Inc
Category: otc | Type: HUMAN OTC DRUG LABEL
Date: 20110610

ACTIVE INGREDIENTS: OCTINOXATE 3 mL/50 mL; TITANIUM DIOXIDE 2.15 mL/50 mL; OCTISALATE 2 mL/50 mL
INACTIVE INGREDIENTS: WATER; DIMETHICONE; CETOSTEARYL ALCOHOL; POLYGLYCERYL-4 ISOSTEARATE; HEXYL LAURATE; SODIUM STEAROYL LACTYLATE; SQUALANE; PHENOXYETHANOL; MICA; METHYLPARABEN; TROLAMINE; GLYCERIN; MAGNESIUM ALUMINUM SILICATE; PROPYLPARABEN; EDETATE TRISODIUM; VITAMIN A PALMITATE; TETRAHEXYLDECYL ASCORBATE; TRIETHOXYCAPRYLYLSILANE; HYALURONATE SODIUM; ALPHA-TOCOPHEROL

BB0906

DESCRIPTION

For all skin types. Sheer, natural coverage. Pure, radiant finish. Pure minerals. Pure comfort. Pure perfection. This microlight mineral tinted moisturizer, infused with minerals, vitamins, and antioxidants brightens and evens out skintone with a hint of sheer, natural color. Instantly transforms skin's appearance with a fresh, luminous glow. SPF 15 sun protection. Oil free. Talc free. Fragrance free.

INDICATIONS AND USAGE

To Use: Smooth on to face before sun exposure.

WARNINGS

WARNING: For external use only. Avoid contact with eyes. Discontinue use if irritation or rash appear. If irritation persists, consult a doctor. Keep out of reach of children. Clinically, dermatologist, and allergy tested.

OTC - ACTIVE INGREDIENT

Active Ingredients: Octinoxate 6.0%, Titanium Dioxide 4.3%, Octisalate 4.0%.

INACTIVE INGREDIENT

Other Ingredients: Water/Aqua/Eau, Dimethicone, Mica, Cetearyl Alcohol, Polyglyceryl-4 Isostearate, Cetyl Dimethicon, Hexyl Laurate, Cetyl PEG/PPG-10/1 Dimethicon, Sodium Stearoyl Lactylate, Squalane, Hydrogenated Polyisobutene, Silene Uniflora Extract, Sodium Hyaluronate, Retinyl Palmitate, Tetrahexyldecyl Ascrobate, Tocopherol, Tocopheryl Acetate, Jojoba Esters, Glycerin, Triethoxycaprylylsilane, Carbomer, Magnesium Aluminum Silicate, Triethanolamine, Trisodium EDTA, Methyparaben, Phenoxyethanol, Propylparaben, Iron Oxides (CI 77491, CI 77492, CI 77499), Titanium Dioxide (CI77891).

DOSAGE & ADMINISTRATION

Smooth on to face.

OTC - KEEP OUT OF REACH OF CHILDREN

Keep out of reach of children.

OTC - PURPOSE

Provides SPF 15 sun protection.

OTC - WHEN USING

Avoid contact with eyes.